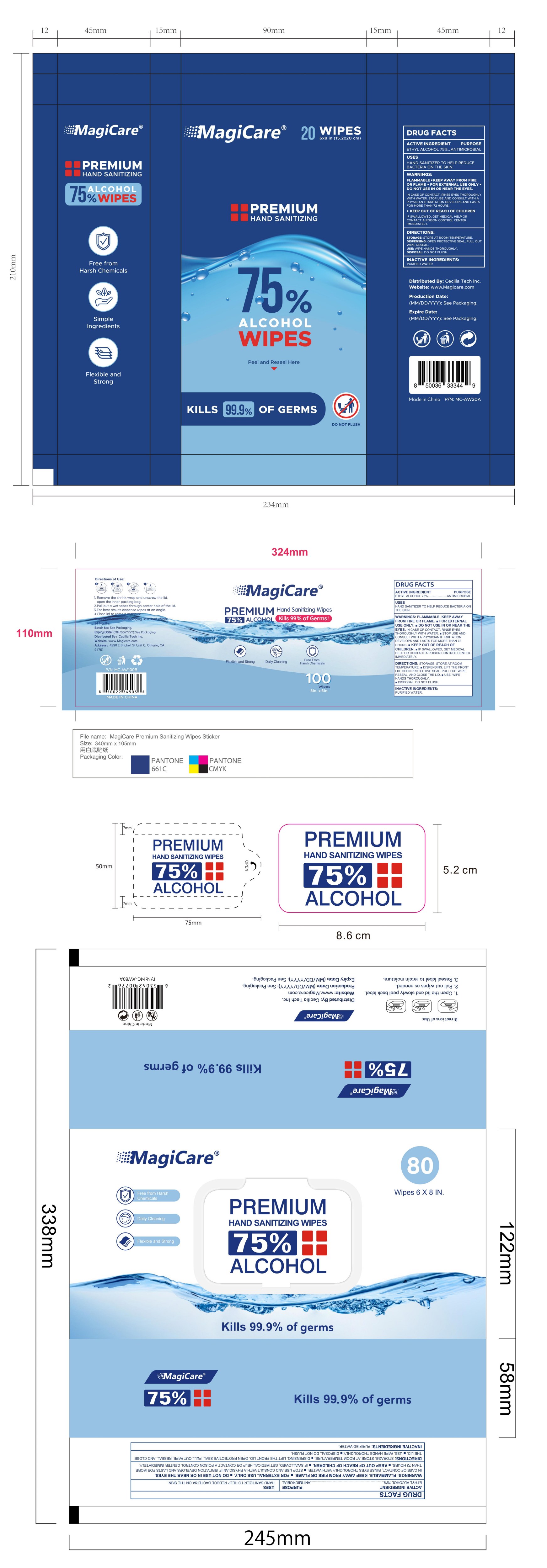 DRUG LABEL: Alcohol Wipes
NDC: 77665-107 | Form: PATCH
Manufacturer: Guangzhou Baihua Co., Ltd
Category: otc | Type: HUMAN OTC DRUG LABEL
Date: 20251124

ACTIVE INGREDIENTS: ALCOHOL 75 mL/100 1
INACTIVE INGREDIENTS: WATER

77665-107

Active Ingredient

Alcohol 75%

Purpose

Antimicrobial

Use

Hand sanitizer to hel reduce bacteria on the skin

Warnings

Flammable, keep away from fire or flame, for external use only, don't use in or near the eyes, keep out of reach of children

Do not use in or near the eyes

When Using

•for external use only, do not use in or near the eyes

Stop Use

• in case of contact, rinse yes thoroughly with water, stop use and consult with a physician if irritation develops and lasts for more than 72 hours

Ask Doctor

• in case of contact, rinse yes thoroughly with water, stop use and consult with a physician if irritation develops and lasts for more than 72 hours

• keep out of reach of children, if swallowed, get medical help or contact a poison control center immediately

Directions

• storage: store at room temperature

• dispensing: open protective seal, pull out wipe, reseal

• use: wipe hands thoroughly For nail fungus,

• disposal: do not fulsh

Other information

•If you are using other drugs, please consult your physician or pharmacist before using this product.
•Shielded from light, sealed, stored in a cool place (not more than 20°C).

Inactive ingredients

purified water

Questions

Tel.400-055-8876